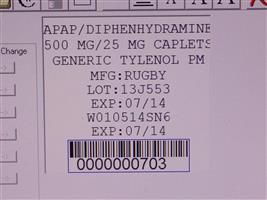 DRUG LABEL: Acetaminophen and Diphenhydramine HCl
                                    
NDC: 68151-0703 | Form: TABLET
Manufacturer: Carilion Materials Management
Category: otc | Type: HUMAN OTC DRUG LABEL
Date: 20171226

ACTIVE INGREDIENTS: ACETAMINOPHEN 500 mg/1 1; DIPHENHYDRAMINE HYDROCHLORIDE 25 mg/1 1
INACTIVE INGREDIENTS: CROSCARMELLOSE SODIUM; FD&C BLUE NO. 1; HYPROMELLOSE, UNSPECIFIED; MICROCRYSTALLINE CELLULOSE; POLYETHYLENE GLYCOL 400; POVIDONE, UNSPECIFIED; STARCH, CORN; SILICON DIOXIDE; STEARIC ACID; TITANIUM DIOXIDE

Acetaminophen and Diphenhydramine HCl Captabs

Active Ingrdient

(in each captab)

PURPOSE

Pain Reliever/Sleep Aid

Uses

Temporarily relieves occasional headaches and minor aches and pains with accompanying sleeplessness.

Warnings

Liver warning: This product contains acetaminophen. Severe liver damage may occur if you take

- more than 8 captabs in 24 hours, which is the maximum daily amount
- with other drugs containing acetaminophen
- 3 or more alcoholic drinks everyday while using this product.

Do not use

- with any other drug containing acetaminophen (prescription or nonprescription). If you are not sure whether a drug contains acetaminophen, ask a doctor or pharmacist.
- with any other drug containing diphenhydramine, even one used on skin
- in children under 12 years of age
  Ask a doctor before use if you have
- liver disease
- glaucoma
- trouble urinating due to an enlarged prostate gland
- a breathing problem such as emphysema or chronic bronchitis
  Ask a doctor or pharmacist before use if you are.
- taking the blood thinning drug warfarin
- taking sedatives or tranquilizers
  When using this product
- marked drowsiness will occur
- avoid alcoholic drinks
- alcohol, sedatives and tranquilizers may increase drowsiness
- do not drive motor vehicle or operate machinery
  Stop use and ask a doctor if
- pain gets worse or lasts more than 10 days
- fever gets worse or lasts more than 3 days
- redness or swelling is present
- any new symptoms appear
- sleeplessness lasts more than 2 weeks. Insomnia may be a sign of serious underlying medical illness.
  If pregnant or breast feeding, ask a health professional before use.
  Keep out of children.
  In case of overdose, get medical help or contact a Poison Control Center right away. Prompt medical attention is critical for adults as well as for children, even if you do not notice any signs or symptoms.

Directions

adults and children 12 years or over:

- take 2 captabs at bedtine if needed
- do not take more than directed

childrens under 12 years do not use

Other Information

Store at room temperature 15°-30°C (59°-86°F)

Inactive Ingredients

Croscarmellose sodium, FD&C blue #1, hypromellose, microcrystalline cellulose, polyethylene glycol 400, povidone, pregelatinized corn starch, silicon dioxide, stearic acid, titanium dioxide.

QUESTIONS

Call 1-800-645-2158, 9 am – 5 pm ET, Monday – Friday.